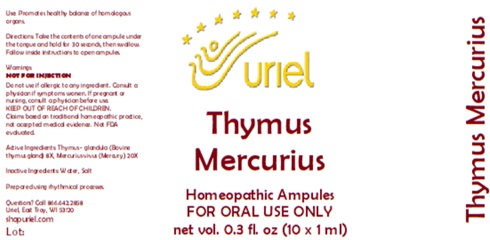 DRUG LABEL: Thymus Mercurius
NDC: 48951-9008 | Form: LIQUID
Manufacturer: Uriel Pharmacy Inc.
Category: homeopathic | Type: HUMAN OTC DRUG LABEL
Date: 20251126

ACTIVE INGREDIENTS: BOS TAURUS THYMUS 8 [hp_X]/1 mL; MERCURY 20 [hp_X]/1 mL
INACTIVE INGREDIENTS: WATER; SODIUM CHLORIDE

Thymus Mercurius

PURPOSE

Use: Promotes healthy balance of homologous organs.

INDICATIONS AND USAGE

FOR ORAL USE ONLY

DOSAGE AND ADMINISTRATION

Directions: Take the contents of one ampule under the tongue and hold for 30 seconds, then swallow. Follow inside instructions to open ampules.

Warnings:
NOT FOR INJECTION
Do not use if allergic to any ingredient. Consult a physician if symptoms worsen. If pregnant or nursing, consult a physician before use.
Claims based on traditional homeopathic practice, not accepted medical evidence. Not FDA evaluated.

KEEP OUT OF REACH OF CHILDREN.

Active Ingredients: Thymus (glandula) 8X, Mercurius vivus 20X

Inactive Ingredients: Water, Salt

Prepared using rhythmical processes.

QUESTIONS

Questions? Call 866.642.2858 Uriel, East Troy, WI 53120 shopuriel.com

Lot: